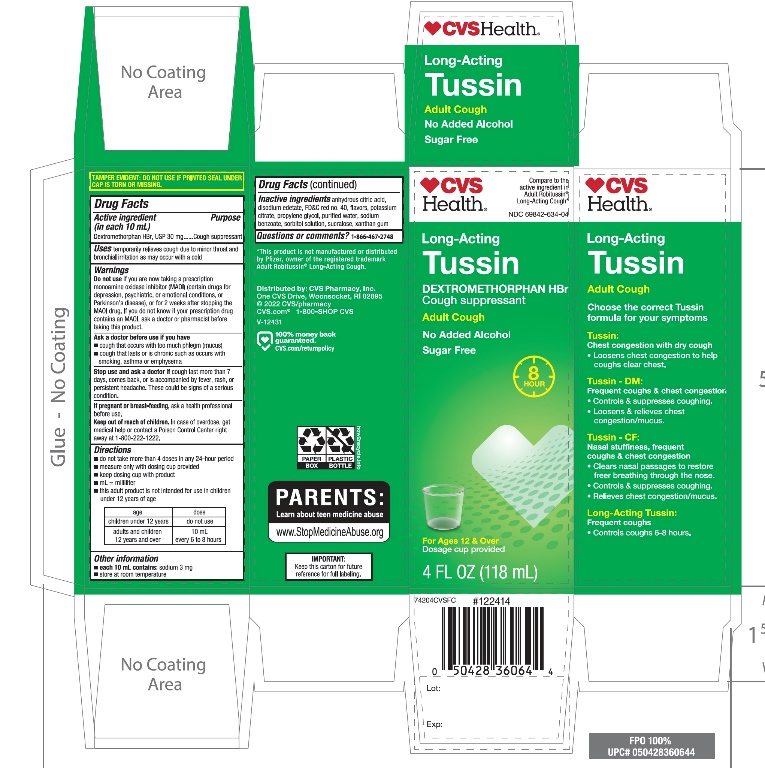 DRUG LABEL: CVS Long Acting Cough
NDC: 69842-634 | Form: LIQUID
Manufacturer: CVS PHARMACY, INC
Category: otc | Type: HUMAN OTC DRUG LABEL
Date: 20251210

ACTIVE INGREDIENTS: DEXTROMETHORPHAN HYDROBROMIDE 30 mg/10 mL
INACTIVE INGREDIENTS: ANHYDROUS CITRIC ACID; EDETATE DISODIUM; FD&C RED NO. 40; POTASSIUM CITRATE; PROPYLENE GLYCOL; WATER; SODIUM BENZOATE; SORBITOL; SUCRALOSE; XANTHAN GUM

CVS Long-Acting Cough Drug Facts

Active ingredient (in each 10 mL)

Dextromethorphan HBr, USP 30 mg

Purpose

Cough suppressant

Uses

- temporarily relieves cough due to minor throat and bronchial irritation as may occur with a cold
- Helps loosen phlegm (mucus) and thin bronchial secretions to drain bronchial tubes

Warnings

Do not use

if you are now taking a prescription monoamine oxidase inhibitor (MAOI) (certain drugs for depression, psychiatric or emotional conditions, or Parkinson’s disease), or for 2 weeks after stopping the MAOI drug. If you do not know if your prescription drug contains an MAOI, ask a doctor or pharmacist before taking this product.

Ask a doctor before use if you have

- cough that occurs with too much phlegm (mucus)
- cough that lasts or is chronic such as occurs with smoking, asthma, or emphysema

Stop use and ask a doctor if

cough lasts more than 7 days, comes back, or is accompanied by fever, rash, or persistent headache. These could be signs of a serious condition.

If pregnant or breast-feeding,

ask a health professional before use.

Keep out of reach of children.

In case of overdose, get medical help or contact a Poison Control Center right away at (1-800-222-1222).

Directions

- do not take more than 4 doses in a 24-hour period
- measure only with dosing cup provided
- keep dosing cup with product
- mL = milliliter
- this adult product is not intended for use in children under 12 years of age

age | dose
adults and children 12 years and over | 10 mL; every 6 to 8 hours
children under 12 years | do not use

Other information

- each 10 ml contains: sodium 3 mg
- store at room temperature

Inactive ingredients

anhydrous citric acid, disodium edetate, FD&C red 40, flavor, potassium citrate, propylene glycol, purified water, sodium benzoate, sorbitol solution, sucralose, xanthan gum

Questions or comments?

1-866-467-2748

Principal Display Panel

NDC# 69842-634-04

*Compare to the active ingredient in Adult Robitussin®Long-Acting Cough*

Long-Acting

Cough

Dextromethorphan HBr (Cough Suppressant)

Relieves:

- Cough

8 Hour Relief

No Added Alcohol

Sugar-Free

For Ages 12 & Over

4 FL OZ (118mL)

*This product is not manufactured or distributed by Pfizer, owner of the registered trademark Adult Robitussin® Long-Acting Cough.

TAMPER EVIDENT: DO NOT USE IF PRINTED SAFETY SEAL ON THE BOTTLE IS BROKEN OR MISSING.

DISTRIBUTED BY